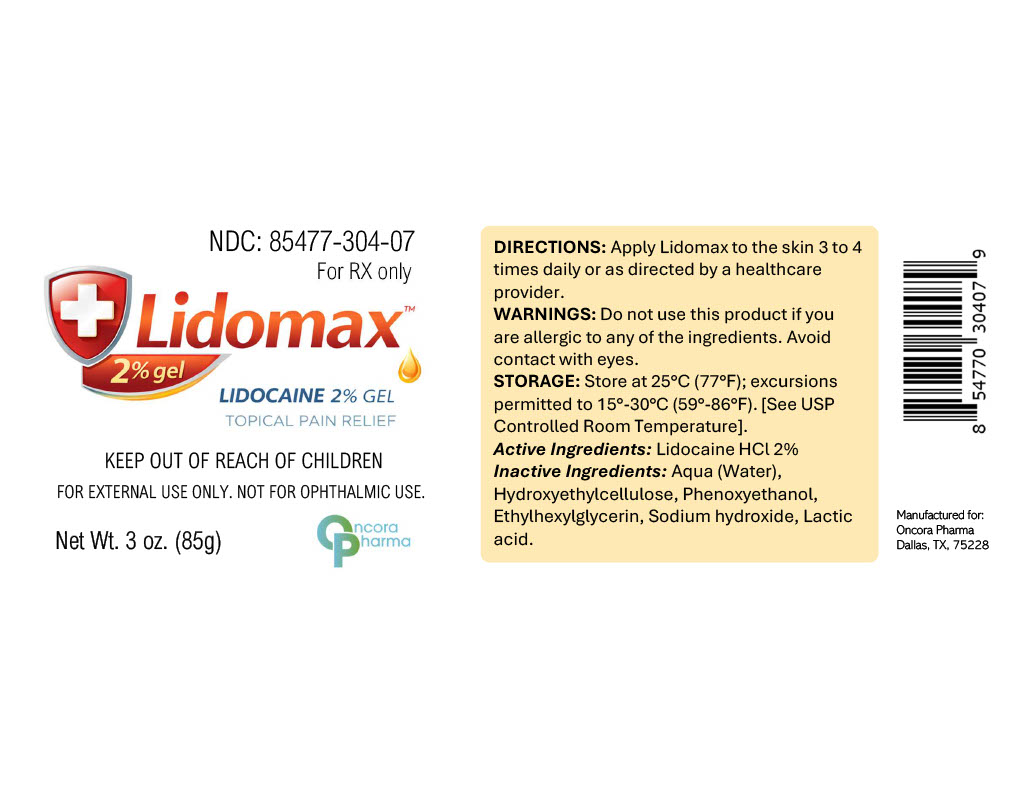 DRUG LABEL: Lidomax
NDC: 85477-304 | Form: GEL
Manufacturer: Oncora Pharma, LLC
Category: prescription | Type: HUMAN PRESCRIPTION DRUG LABEL
Date: 20260227

ACTIVE INGREDIENTS: LIDOCAINE 20 mg/1 g
INACTIVE INGREDIENTS: WATER; HYDROXYETHYLCELLULOSE; PHENOXYETHANOL; ETHYLHEXYLGLYCERIN; SODIUM HYDROXIDE; LACTIC ACID

Lidomax™ (Lidocaine Hydrochloride) Topical Gel 2%

DESCRIPTION

Lidomax™ is a topical gel containing Lidocaine Hydrochloride 2%, a local anesthetic. It is intended for topical application to intact skin.

INDICATIONS AND USAGE

Lidomax™ is indicated for topical analgesia as directed by a healthcare provider.

WARNINGS

For external use only. Not for ophthalmic use. Avoid contact with eyes. Do not use if allergic to lidocaine or any components of the formulation. Keep out of reach of children.

DOSAGE AND ADMINISTRATION

Apply a thin layer to the affected area 3 to 4 times daily or as directed by a healthcare provider. For external use only.

HOW SUPPLIED

Lidomax™ (Lidocaine HCl 2%) is supplied as a clear topical gel in a 3 oz (85 g) tube. NDC 85477-304-07

PRINCIPAL DISPLAY PANEL

Store at 25°C (77°F); excursions permitted to 15°–30°C (59°–86°F).
[See USP Controlled Room Temperature].
Keep container tightly closed.

pdp